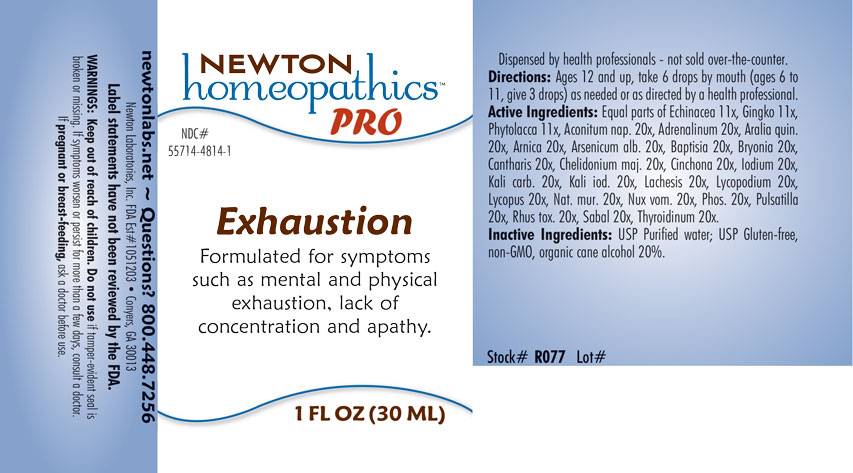 DRUG LABEL: Exhaustion
NDC: 55714-4814 | Form: LIQUID
Manufacturer: Newton Laboratories, Inc.
Category: homeopathic | Type: HUMAN OTC DRUG LABEL
Date: 20201203

ACTIVE INGREDIENTS: ACONITUM NAPELLUS 20 [hp_X]/1 mL; EPINEPHRINE 20 [hp_X]/1 mL; AMERICAN GINSENG 20 [hp_X]/1 mL; ARNICA MONTANA 20 [hp_X]/1 mL; ARSENIC TRIOXIDE 20 [hp_X]/1 mL; BAPTISIA TINCTORIA 20 [hp_X]/1 mL; BRYONIA ALBA ROOT 20 [hp_X]/1 mL; LYTTA VESICATORIA 20 [hp_X]/1 mL; CHELIDONIUM MAJUS 20 [hp_X]/1 mL; CINCHONA OFFICINALIS BARK 20 [hp_X]/1 mL; IODINE 20 [hp_X]/1 mL; POTASSIUM CARBONATE 20 [hp_X]/1 mL; POTASSIUM IODIDE 20 [hp_X]/1 mL; LACHESIS MUTA VENOM 20 [hp_X]/1 mL; LYCOPODIUM CLAVATUM SPORE 20 [hp_X]/1 mL; LYCOPUS VIRGINICUS 20 [hp_X]/1 mL; SODIUM CHLORIDE 20 [hp_X]/1 mL; STRYCHNOS NUX-VOMICA SEED 20 [hp_X]/1 mL; PHOSPHORUS 20 [hp_X]/1 mL; ANEMONE PULSATILLA 20 [hp_X]/1 mL; TOXICODENDRON PUBESCENS LEAF 20 [hp_X]/1 mL; SAW PALMETTO 20 [hp_X]/1 mL; THYROID, UNSPECIFIED 20 [hp_X]/1 mL; ECHINACEA, UNSPECIFIED 11 [hp_X]/1 mL; GINKGO 11 [hp_X]/1 mL; PHYTOLACCA AMERICANA ROOT 11 [hp_X]/1 mL
INACTIVE INGREDIENTS: WATER; ALCOHOL

Exhaustion 4814L

INDICATIONS & USAGE SECTION

Formulated for symptoms of mental and physical exhaustion, lack of concentration and apathy.

DOSAGE & ADMINISTRATION SECTION

Directions: Ages 12 and up, take 6 drops by mouthy (ages 6 to 11, give 3 drops) as needed or as directed by a health professional.

OTC - ACTIVE INGREDIENT SECTION

Active Ingredients: Equal parts of Echinacea 11x, Gingko biloba 11x, Phytolacca decandra 11x, Aconitum napellus 20x, Adrenalinum 20x, Aralia quinquefolia 20x, Arnica montana 20x, Arsenicum album 20x, Baptisia tinctoria 20x, Bryonia 20x, Cantharis 20x, Chelidonium majus 20x, Cinchona officinalis 20x, Iodium 20x, Kali carbonicum 20x, Kali iodatum 20x, Lachesis mutus 20x, Lycopodium clavatum 20x, Lycopus virginicus 20x, Natrum muriaticum 20x, Nux vomica 20x, Phosphorus 20x, Pulsatilla 20x, Rhus toxicodendron 20x, Sabal serrulata 20x, Thyroidinum 20x.

OTC - PURPOSE SECTION

Formulated for symptoms such as mental and physical exhaustion, lack of concentration and apathy.

INACTIVE INGREDIENT SECTION

Inactive Ingredients: USP Purified Water; USP Gluten-free, non-GMO, organic cane alcohol 20%.

QUESTIONS SECTION

newtonlabs.net – Questions? 800.448.7256

Newton Laboratories, Inc. FDA Est # 1051203 - Conyers, GA 30013

WARNINGS SECTION

WARNINGS: Keep out of reach of children. Do not use if tamper-evident seal is broken or missing. If symptoms worsen or persist for more than a few days, consult a doctor. If pregnant or breast-feeding, ask a doctor before use.

OTC - PREGNANCY OR BREAST FEEDING SECTION

If pregnant or breast-feeding, ask a doctor before use.

OTC - KEEP OUT OF REACH OF CHILDREN SECTION

Keep out of reach of children.